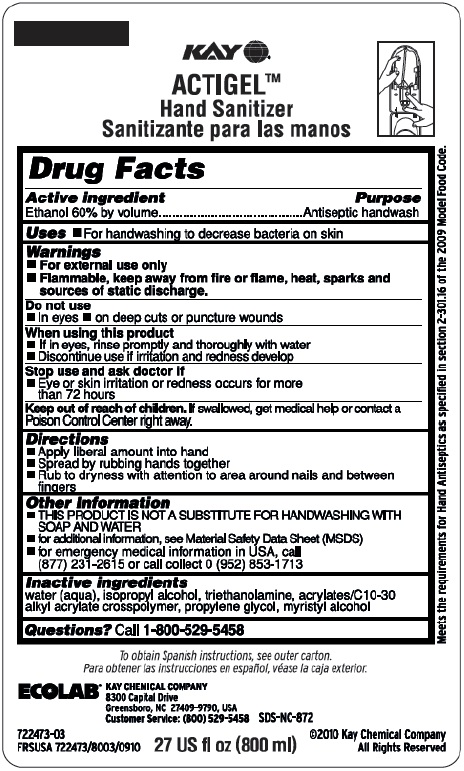 DRUG LABEL: Kay Actigel Hand Sanitizer
NDC: 47593-679 | Form: SOLUTION
Manufacturer: Ecolab Inc.
Category: otc | Type: HUMAN OTC DRUG LABEL
Date: 20251231

ACTIVE INGREDIENTS: ALCOHOL 60 mL/100 mL
INACTIVE INGREDIENTS: WATER; ISOPROPYL ALCOHOL; TROLAMINE; CARBOMER COPOLYMER TYPE B (ALLYL PENTAERYTHRITOL CROSSLINKED); PROPYLENE GLYCOL; MYRISTYL ALCOHOL

Drug Facts

Active ingredient

Ethanol 60% by volume

Purpose

Antiseptic handwash

Uses

- For handwashing to decrease bacteria on the skin

Warnings

- For external use only
- Flammale, keep away from fire or flame, heat, sparks and sources of static discharge.

Do not use

- In eyes
- On deep cuts or puncture wounds

When using this product

- If in eyes, rinse promptly and thoroughly with water
- Discontinue use if irritation and redness develop

Stop use and ask a doctor if

- Eye or skin irritation and redness persist for more than 72 hours

Keep out of reach of children. If swallowed, get medical help or contact a Poison Control Center right away.

Directions

- Apply liberal amount into hand
- Spread by rubbing hands together
- Rub to dryness with attention to area around nails and between fingers

Other information

- THIS PRODUCT IS NOT A SUBSTITUTE FOR HANDWASHING WITH SOAP AND WATER
- For additional information, see Material Safety Data Sheet (MSDS)
- For emergency medical information in the USA call 1 (877) 231-2615 or call collect 0 (952)853-1713

Inactive ingredients

water (aqua), isopropyl alcohol, triethanolamine, acrylates/C10-C30 alkyl acrylate crosspolymer, propylene glycol, myristyl alcohol

Questions? call 1-800-529-5458

Principal Display Panel/Representative Label

Kay

Actigel

Hand Sanitizer

To obtain instruction in Spanish, see outer carton.

ECOLAB

KAY CHEMICAL COMPANY

8300 Capital Drive

Greensboro, NC 27409-9790, USA

Customer Service: (800) 529-5458

SDS-NC-872

27 US fl oz (800 ml)

722473-03

FRSUSA 722473/8003/0910

©2010 Kay Chemical Company

All Rights Reserved